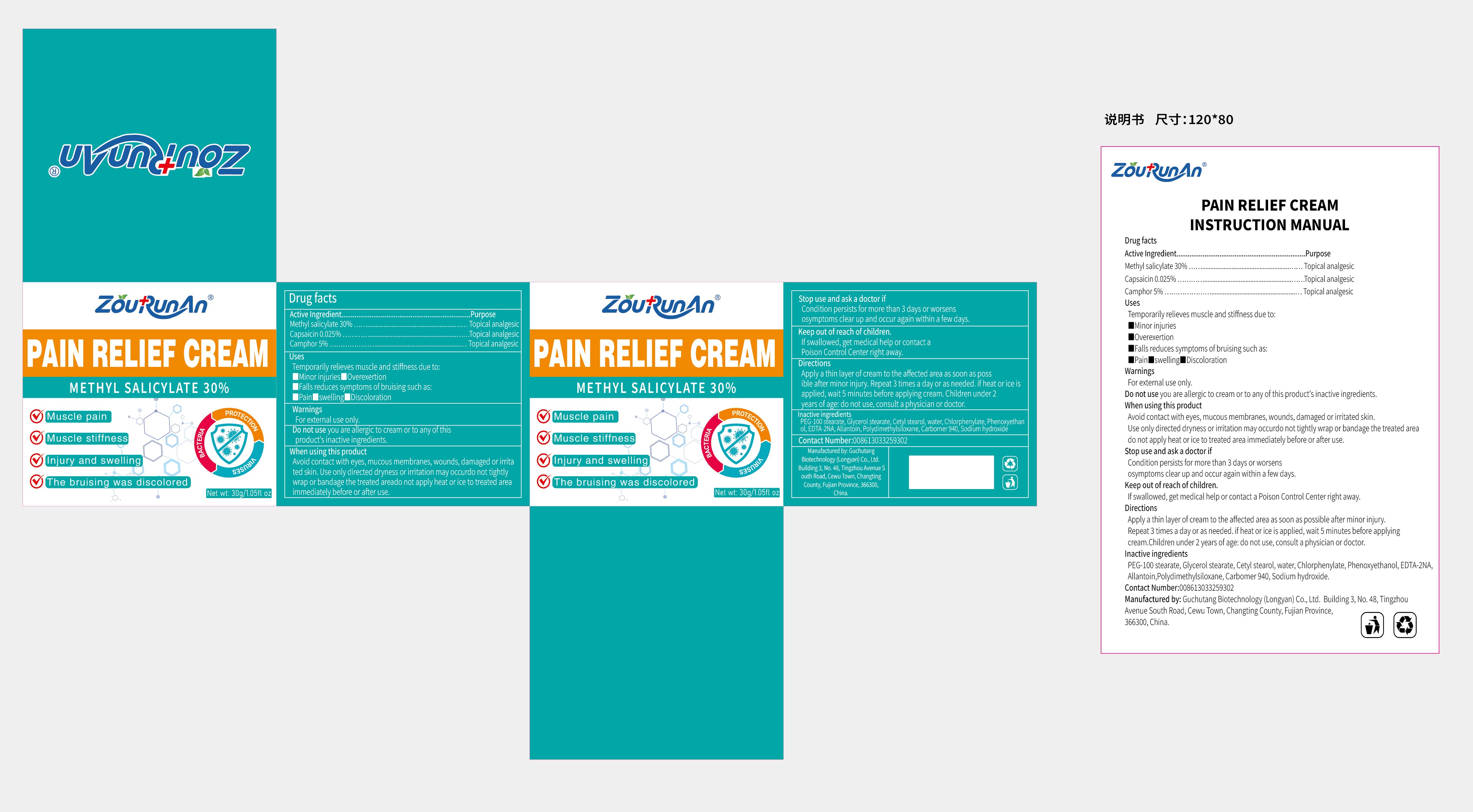 DRUG LABEL: zourunan PAIN RELIEF
NDC: 87083-007 | Form: CREAM
Manufacturer: Guchutang Biotechnology (Longyan) Co., Ltd
Category: otc | Type: HUMAN OTC DRUG LABEL
Date: 20251022

ACTIVE INGREDIENTS: METHYL SALICYLATE 30 g/100 g; CAPSAICIN 0.025 g/100 g; CAMPHOR (NATURAL) 5 g/100 g
INACTIVE INGREDIENTS: CARBOMER 940; GLYCERYL MONOSTEARATE; CETOSTEARYL ALCOHOL; SODIUM HYDROXIDE; PEG-60 STEARATE; WATER; PHENOXYETHANOL; EDETATE CALCIUM DISODIUM; ALLANTOIN; DIMETHICONE

87083-007

Active Ingredient

Methyl salicylate 30%
Capsaicin 0.025%
Camphor 5%

Purpose

Topical analgesic

Use

Temporarily relieves muscle and stiffness due to:
■minor injuries
■overexertion
■falls reduces symptoms of bruising such as:
■pain■swelling■discoloration

Warnings

For external use only.

Do not use

you are allergic to cream or to any of this product's inactive ingredients.

When Using

Avoid contact with eyes, mucous membranes, wounds, damaged or irritated skin. Use only directed dryness or irritation may occurdo not tightly wrap or bandage the treated areado not apply heat or ice to treated area immediately before or after use.

Stop Use

Condition persists for more than 3 days or worsens osymptoms clear up and occur again within a few days.

Ask Doctor

Condition persists for more than 3 days or worsens osymptoms clear up and occur again within a few days.

Keep Out Of Reach Of Children

If swallowed, get medical help or contact a Poison Control Center right away.

Directions

Apply a thin layer of cream to the affected area as soon as possible after minor injury.Repeat 3 times a day or as needed. if heat or ice is applied, wait 5 minutes before applying cream.Children under 2 years of age: do not use, consult a physician or doctor.

Inactive ingredients

PEG-100 stearate, Glycerol stearate, Cetyl stearol, water, Chlorphenylate, Phenoxyethanol, EDTA-2NA, Allantoin, Polydimethylsiloxane, Carbomer 940, Sodium hydroxide.